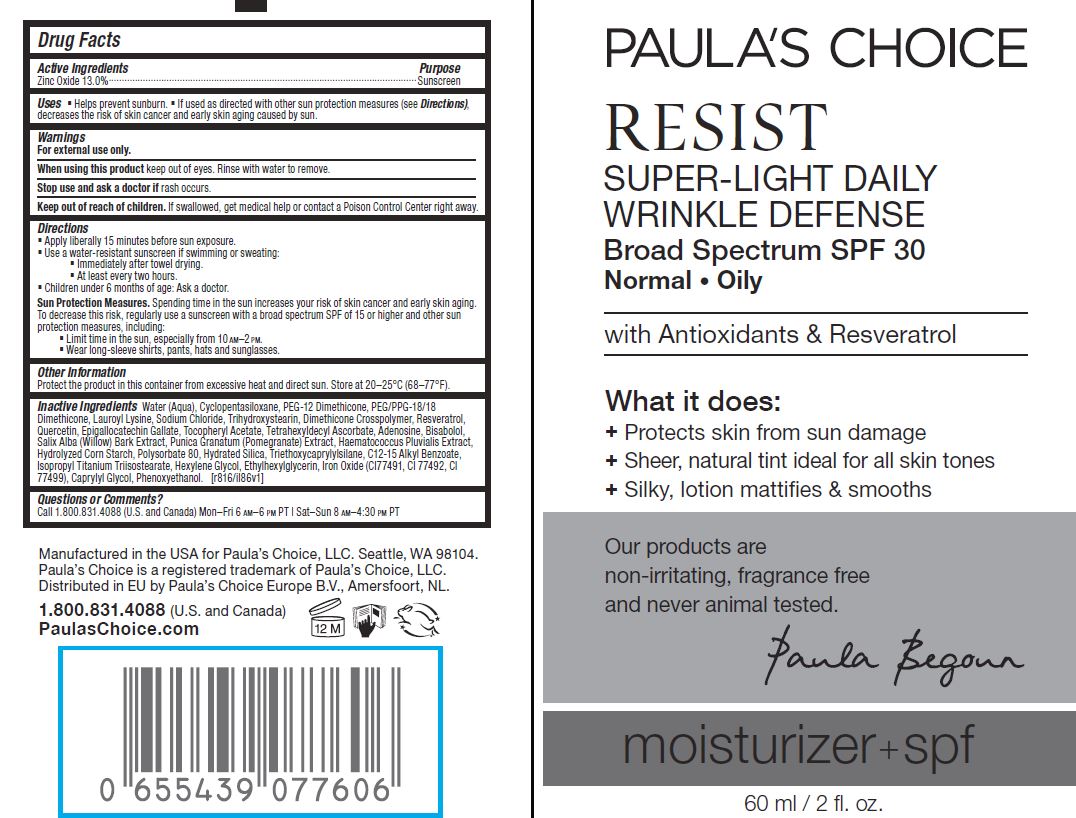 DRUG LABEL: Resist Wrinkle Defense SPF 30
NDC: 56152-5003 | Form: CREAM
Manufacturer: Cosmetic Enterprises Ltd
Category: otc | Type: HUMAN OTC DRUG LABEL
Date: 20251014

ACTIVE INGREDIENTS: ZINC OXIDE 13 g/100 mL
INACTIVE INGREDIENTS: WATER; CYCLOMETHICONE 5; PEG-12 DIMETHICONE; PEG/PPG-18/18 DIMETHICONE; LAUROYL LYSINE; SODIUM CHLORIDE; TRIHYDROXYSTEARIN; DIMETHICONE CROSSPOLYMER (450000 MPA.S AT 12% IN CYCLOPENTASILOXANE); RESVERATROL; QUERCETIN; EPIGALLOCATECHIN GALLATE; .ALPHA.-TOCOPHEROL ACETATE; TETRAHEXYLDECYL ASCORBATE; ADENOSINE; LEVOMENOL; SALIX ALBA BARK; PUNICA GRANATUM ROOT BARK; HAEMATOCOCCUS PLUVIALIS; POLYSORBATE 80; HYDRATED SILICA; TRIETHOXYCAPRYLYLSILANE; ALKYL (C12-15) BENZOATE; ISOPROPYL TITANIUM TRIISOSTEARATE; HEXYLENE GLYCOL; ETHYLHEXYLGLYCERIN; FERRIC OXIDE RED; FERRIC OXIDE YELLOW; FERROSOFERRIC OXIDE; CAPRYLYL GLYCOL; PHENOXYETHANOL

Resist Super-Light Daily Wrinkle Defense Broad Spectrum SPF 30

Active Ingredients Purpose

Zinc Oxide 13.0% ................. Sunscreen

Uses

- Helps prevent sunburn
- If used as directed with otehr sun protection measures (see Directions), decreases the risk of skin cancer and early skin aging caused by the sun

Keep out of reach of children. If swallowed, get medical help or contact a Poison Control Center right away

Stop use and ask a doctor ifrash occurs

Warnings

- For external use only
- When using this product keep out of eyes. Rinse with water to remove

Directions

- Apply liberally 15 minutes before sun exposure
- Use a water-resistant sunscreen if swimming or seating:
- Immediately after towel dyring
- At least every two hours
- Children under 6 months of age: Ask a doctor

Sun Protection Measures. Spending time in the sun increases your risk of skin cancer and early skin aging. To decrease this risk, regularly use a sunscreen with a broad spectrum SPF of 15 or higher and other sun protection measures, including:

- Limit tim in the sun, especially from 10a.m.-2p.m.
- Wear long-sleeve shirts, pants, hats and sunglasses

INACTIVE INGREDIENT

Water (Aqua), Cyclopentasiloxane, PEG-12 Dimethicone, PEG/PPG-18/18 Dimethicone, Lauroyl Lysine, Sodium Chloride, Trihydroxystearin, Dimethicone Crosspolymer, Resveratrol, Quercetin, Epigalloactechin Gallate, Tocopheryl Acetate, Tetrahexyldecyl Ascorbate, Adenosine, Bisabolol, Salix Alba (Willow) Bark Extract, Punica Granatum (Pomegranate) Extract, Haematococus Pluvialis Extract, Hydrolyzed Corn Starch, Polysorbate 80, Hydrated Silica, Triethoxycaprylylsilane, C12-15 Alkyl Benzoate, Isopropyl Titanium Triisostearate, Hexylene Glycol, Ethylhexylglycerin, Iron Oxide (CI 77491, CI 77492, CI 77499), Caprylyl Glycol, Phenoxyethanol

PACKAGE LABEL

PAULA'S CHOICE

RESIST

Super-Light Daily

Wrinkle Defense

Broad Spectrum SPF 30

60 ml / 2 fl. oz.